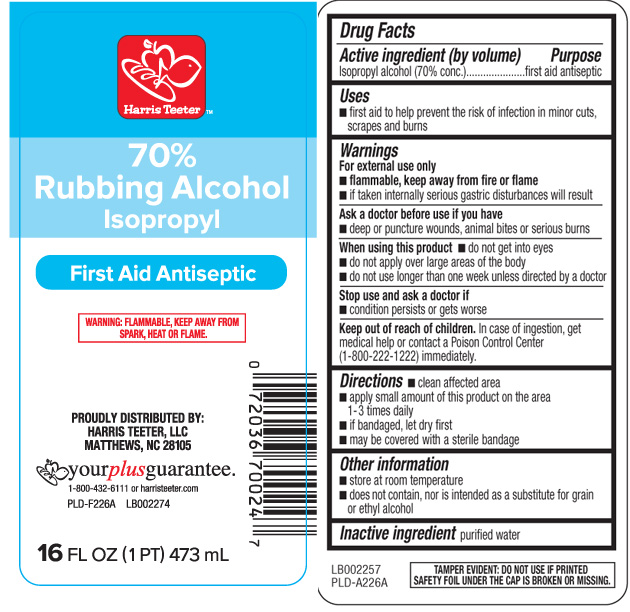 DRUG LABEL: Rubbing Alcohol
NDC: 69256-275 | Form: LIQUID
Manufacturer: Harris Teeter, LLC
Category: otc | Type: HUMAN OTC DRUG LABEL
Date: 20250207

ACTIVE INGREDIENTS: ISOPROPYL ALCOHOL 70 mL/100 mL
INACTIVE INGREDIENTS: WATER

Drug Facts

Active Ingredients

Isopropyl alcohol (70% conc.)

Purpose

first aid antiseptic

Uses

- first aid to help prevent the risk of infection in minor cuts, scrapes and burns

Warnings

For external use only

- flammable, keep away from fire or flame
- if taken internally serious gastric disturances will result

Ask a doctor before use if you have

- deep or puncture wounds, animal bites or serious burns

When using this product

- do not get into eyes
- do not apply over large areas of the body
- do not use longer than one week unless directed by a doctor

Stop use and ask a doctor if

- conditions persists or gets worse

Keep out of reach of children

In case of ingestion, get medical help or contact a Poison Control Center (1-800-222-1222) immediately.

Directions

- clean affected area
- apply small amount of this product on the area 1-3 times daily
- if bandaged, let dry first
- may be covered with a sterile bandage

Other Information

- store at room temperature
- does not contain, nor is intended as a substitute for grain or ehyl alcohol

Inactive Ingredient

purified water

Principal Display Panel

70% Rubbing Alcohol

Isopropyl

First Aid Antiseptic

WARNING: FLAMMABLE, KEEP AWAY FROM SPARK, HEAT OR FLAME.

PROUDLY DISTRIBUTED BY:

HARRIS TEETER, LLC

MATTHEWS, NC 28105

1-800-432-6111 or harristeeter.com

FL OZ (mL)

TAMPER EVIDENT: DO NOT USE IF PRINTED SAFTEY FOIL UNDER THE CAP IS BROKEN OR MISSING.

Product Label

Harris Teeter 70% Rubbing Alcohol Isopropyl